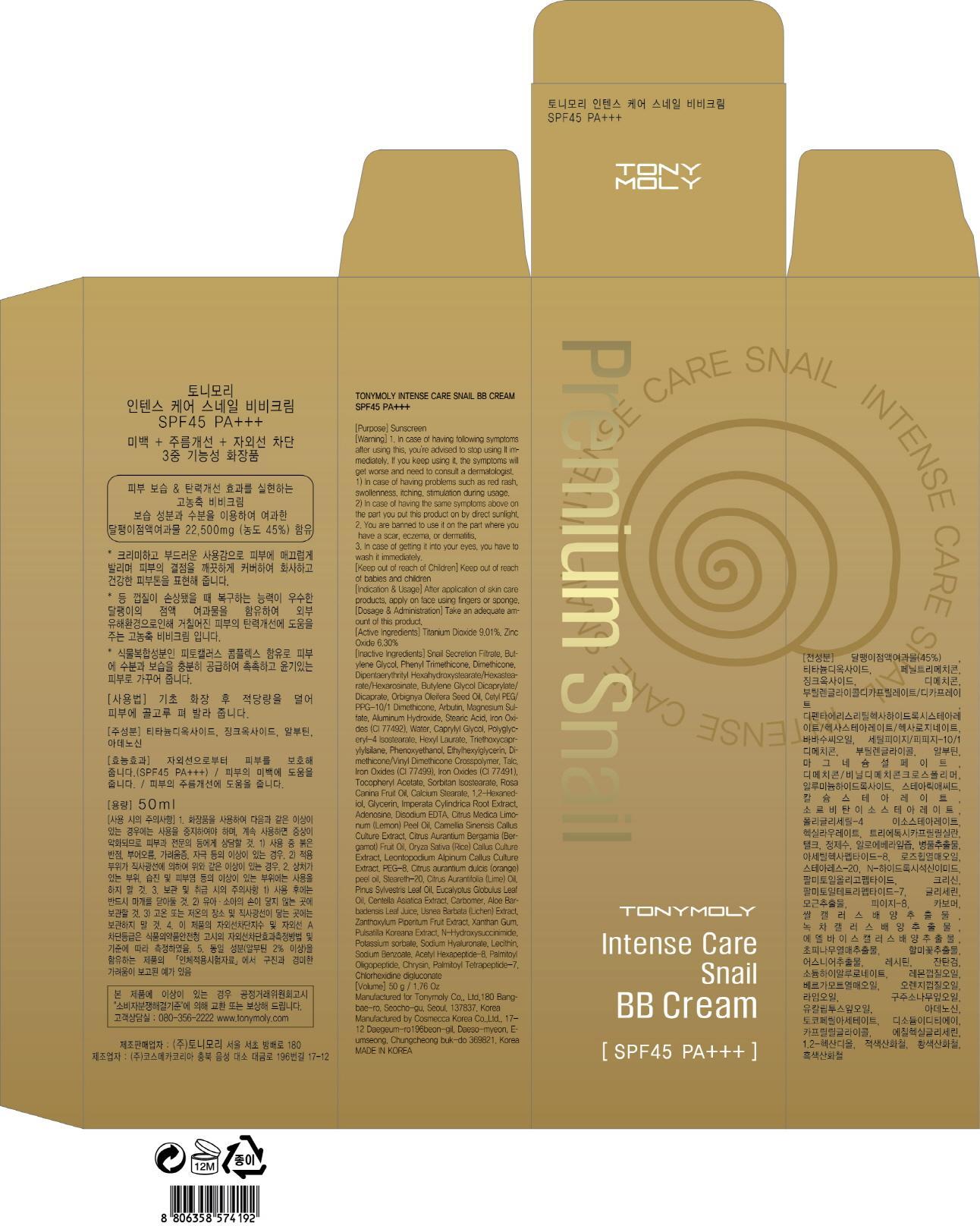 DRUG LABEL: TONYMOLY INTENSE CARE SNAIL BB
NDC: 59078-051 | Form: CREAM
Manufacturer: Tonymoly Co., Ltd.
Category: otc | Type: HUMAN OTC DRUG LABEL
Date: 20150303

ACTIVE INGREDIENTS: Titanium Dioxide 4.50 mg/50 mL; Zinc Oxide 3.15 mg/50 mL
INACTIVE INGREDIENTS: Butylene Glycol; Phenyl Trimethicone

ACTIVE INGREDIENT

Active Ingredients: Titanium Dioxide 9.01%, Zinc Oxide 6.30%

INACTIVE INGREDIENT

Inactive Ingredients: Snail Secretion Filtrate, Butylene Glycol, Phenyl Trimethicone, Dimethicone, Dipentaerythrityl Hexahydroxystearate/Hexastearate/Hexarosinate, Butylene Glycol Dicaprylate/Dicaprate, Orbignya Oleifera Seed Oil, Cetyl PEG/PPG-10/1 Dimethicone, Arbutin, Magnesium Sulfate, Aluminum Hydroxide, Stearic Acid, Iron Oxides (CI 77492), Water, Caprylyl Glycol, Polyglyceryl-4 Isostearate, Hexyl Laurate, Triethoxycaprylylsilane, Phenoxyethanol, Ethylhexylglycerin, Dimethicone/Vinyl Dimethicone Crosspolymer, Talc, Iron Oxides (CI 77499), Iron Oxides (CI 77491), Tocopheryl Acetate, Sorbitan Isostearate, Rosa Canina Fruit Oil, Calcium Stearate, 1,2-Hexanediol, Glycerin, Imperata Cylindrica Root Extract, Adenosine, Disodium EDTA, Citrus Medica Limonum (Lemon) Peel Oil, Camellia Sinensis Callus Culture Extract, Citrus Aurantium Bergamia (Bergamot) Fruit Oil, Oryza Sativa (Rice) Callus Culture Extract, Leontopodium Alpinum Callus Culture Extract, PEG-8, Citrus aurantium dulcis (orange) peel oil, Steareth-20, Citrus Aurantifolia (Lime) Oil, Pinus Sylvestris Leaf Oil, Eucalyptus Globulus Leaf Oil, Centella Asiatica Extract, Carbomer, Aloe Barbadensis Leaf Juice, Usnea Barbata (Lichen) Extract, Zanthoxylum Piperitum Fruit Extract, Xanthan Gum, Pulsatilla Koreana Extract, N-Hydroxysuccinimide, Potassium sorbate, Sodium Hyaluronate, Lecithin, Sodium Benzoate, Acetyl Hexapeptide-8, Palmitoyl Oligopeptide, Chrysin, Palmitoyl Tetrapeptide-7, Chlorhexidine digluconate

PURPOSE

Purpose: Sunscreen

WARNINGS

Warning: 1. In case of having following symptoms after using this, you're advised to stop using it immediately. If you keep using it, the symptoms will get worse and need to consult a dermatologist. 1) In case of having problems such as red rash, swollenness, itching, stimulation during usage. 2) In case of having the same symptoms above on the part you put this product on by direct sunlight. 2. You are banned to use it on the part where you have a scar, eczema, or dermatitis. 3. In case of getting it into your eyes, you have to wash it immediately.

Keep out of reach of Children: Keep out of reach of babies and children

INDICATIONS & USAGE

Indication & Usage: After application of skin care products, apply on face using fingers or sponge.

DOSAGE & ADMINISTRATION

Dosage & Administration: Take an adequate amount of this product.

PACKAGE LABEL.PRINCIPAL DISPLAY PANEL

Image of carton